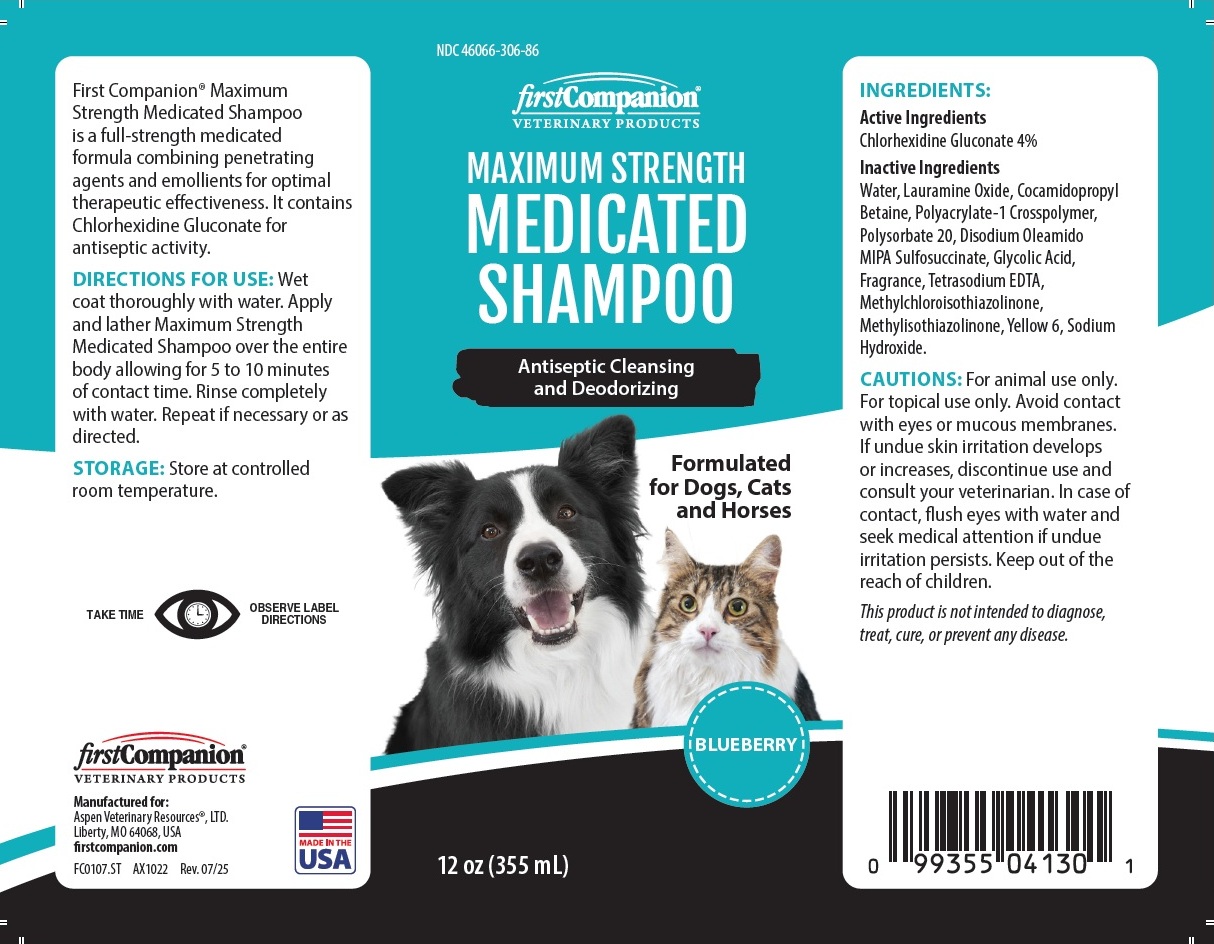 DRUG LABEL: firstCompanion MAXIMUM STRENGTH MEDICATED
NDC: 46066-306 | Form: SHAMPOO
Manufacturer: Aspen Veterinary Resources, Ltd.
Category: animal | Type: OTC ANIMAL DRUG LABEL
Date: 20250926

ACTIVE INGREDIENTS: CHLORHEXIDINE GLUCONATE 4 g/100 mL
INACTIVE INGREDIENTS: WATER; LAURAMINE OXIDE; COCAMIDOPROPYL BETAINE; POLYACRYLATE-1 CROSSPOLYMER; POLYSORBATE 20; DISODIUM OLEAMIDO MIPA-SULFOSUCCINATE; GLYCOLIC ACID; EDETATE SODIUM; METHYLCHLOROISOTHIAZOLINONE; METHYLISOTHIAZOLINONE; FD&C YELLOW NO. 6; SODIUM HYDROXIDE

firstCompanion® VETERINARY PRODUCTS MAXIMUM STRENGTH MEDICATED SHAMPOO

Active Ingredients

Chlorhexidine Gluconate 4%

Inactive Ingredients

Water, Lauramine Oxide, Cocamidopropyl Betaine, Polyacrylate-1 Crosspolymer, Polysorbate 20, Disodium Oleamido MIPA Sulfosuccinate, Glycolic Acid, Fragrance, Tetrasodium EDTA, Methylchloroisothiazolinone, Methylisothiazolinone, Yellow 6, Sodium Hydroxide.

CAUTIONS:

For animal use only. For topical use only. Avoid contact with eyes or mucous membranes. If undue skin irritation develops or increases, discontinue use and consult your veterinarian. In case of contact, flush eyes with water and seek medical attention if undue irritation persists. Keep out of the reach of children.
This product is not intended to diagnose, treat, cure, or prevent any disease.

DIRECTIONS FOR USE:

Wet coat thoroughly with water. Apply and lather Maximum Strength Medicated Shampoo over the entire body allowing for 5 to 10 minutes of contact time. Rinse completely with water. Repeat if necessary or as directed.

STORAGE:

Store at controlled room temperature.

Antiseptic Cleansing and Deodorizing

Formulated for Dogs, Cats and Horses

BLUEBERRY

First Companion® Maximum Strength Medicated Shampoo is a full-strength medicated formula combining penetrating agents and emollients for optimal therapeutic effectiveness. It contains Chlorhexidine Gluconate for antiseptic activity.

TAKE TIME

OBSERVE LABEL DIRECTIONS

Manufactured for:
Aspen Veterinary Resources®, LTD.
Liberty, MO 64068, USA

firstcompanion.com

MADE IN THE USA